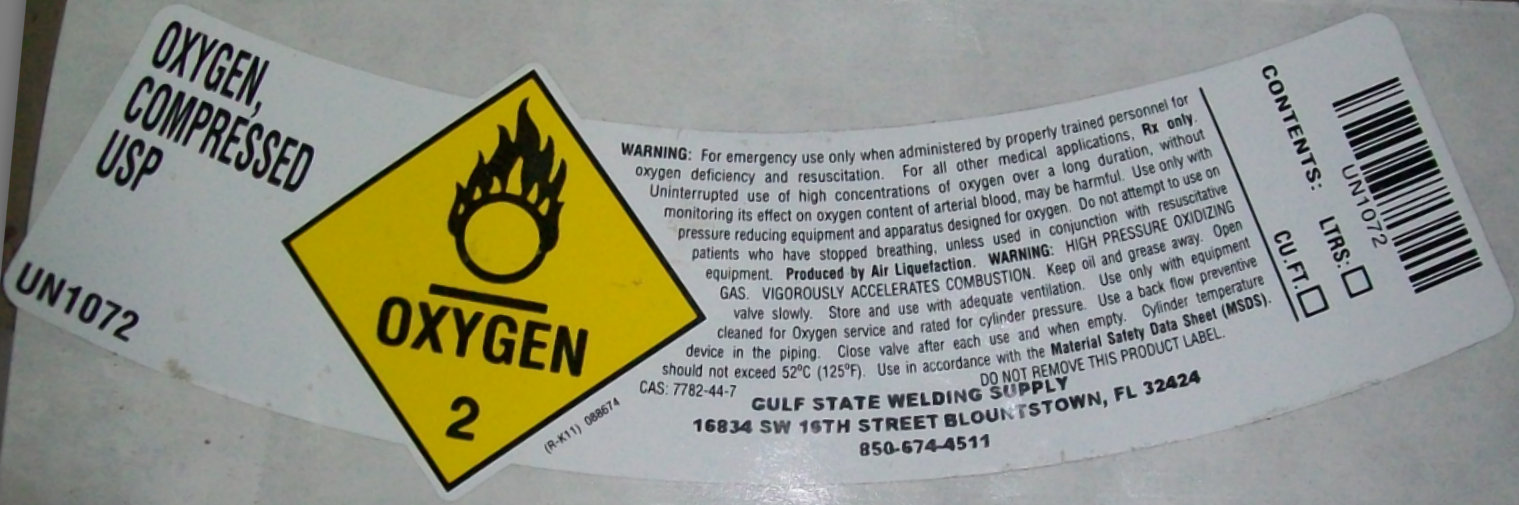 DRUG LABEL: Oxygen, Compressed
NDC: 61336-001 | Form: LIQUID
Manufacturer: Gulf State Chemical and Welding Supply Inc.
Category: prescription | Type: HUMAN PRESCRIPTION DRUG LABEL
Date: 20191226

ACTIVE INGREDIENTS: OXYGEN 1 L/1 L

Oxygen, Compressed USP

Oxygen, Compressed USP 0.49 Liters (15C/F) (61336-001-00) | Oxygen, Compressed USP 0.82 Liters (25C/F) (61336-001-01) | Oxygen, Compressed USP 4.11 Liters (125C/F) (61336-001-02) | Oxygen, Compressed USP 9.24 Liters (281C/F) (61336-001-03) | Oxygen, Compressed USP 180 Liters (61336-001-04)

WARNING: For emergency use only when administered by properly trained personnel for oxygen deficiency and resuscitation. For all other medical application, Rx only.

Uninterrupted use of high concentrations of oxygen over a long duration, without monitoring its effect on oxygen content of arterial blood, may be harmful. Use only with pressure reducing equipment and apparatus designed for oxygen. Do not attempt to use on patients who have stopped breathing, unless used in conjunction with resuscitative equipment.

Produced by Air Liquefaction.

WARNING: HIGH PRESSURE OXIDIZING GAS. VIGOROUSLY ACCELERATES COMBUSTION.

Keep oil and grease away. Open valve slowly. Store and use with adequate ventilation. Use only with equipment cleaned for Oxygen service and rated for cylinder pressure. Use a back flow preventive device in the piping. Close valve after each use and when empty. Cylinder temperature should not exceed 52 degrees C (125 degrees F)

Use in accordance with the Material Safety Data Sheet (MSDS).

GULF STATE WELDING SUPPLY

16834 SW 16TH STREET BLOUNTSTOWN, FL 32424

850-674-4511